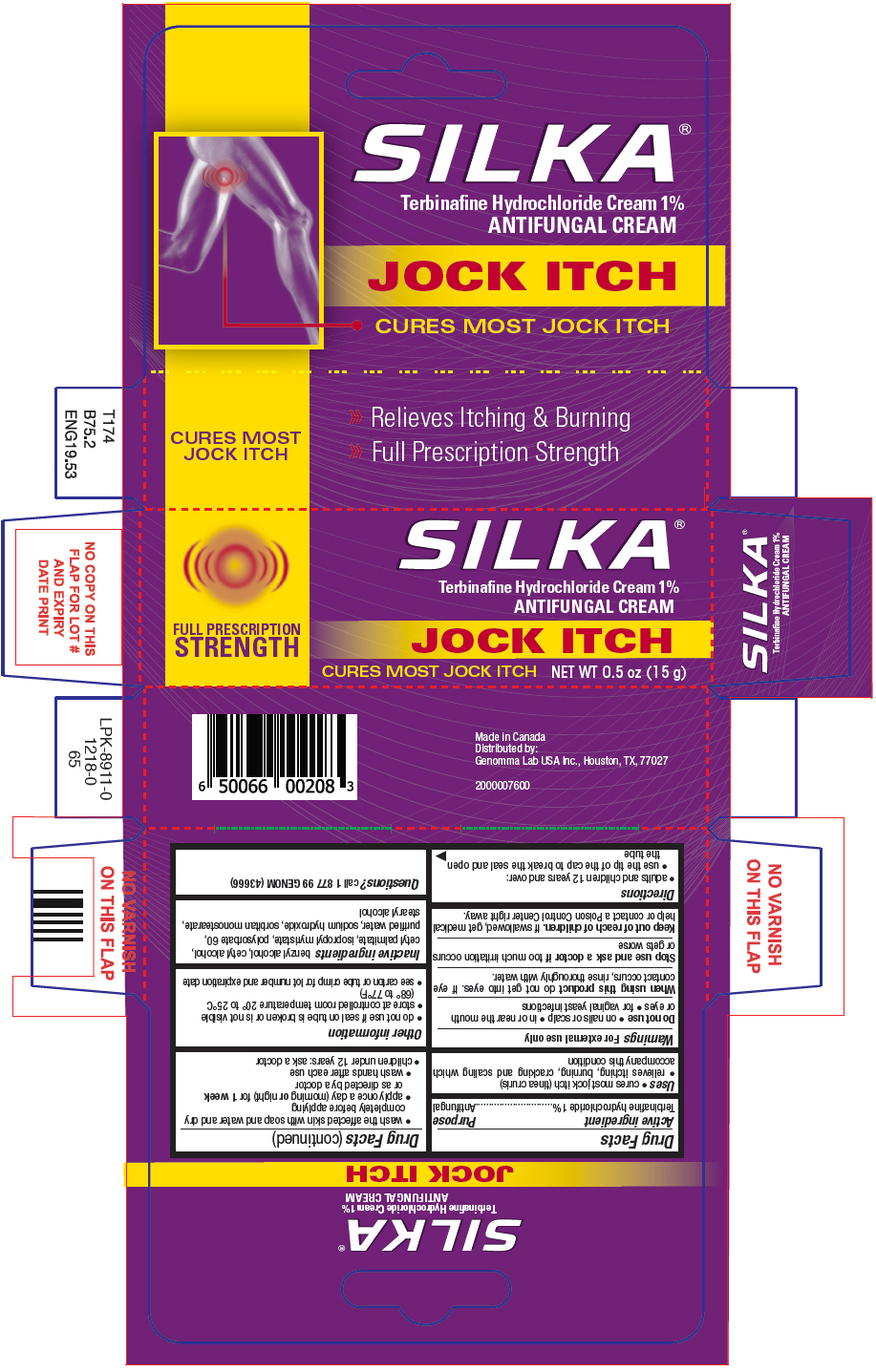 DRUG LABEL: Silka 

NDC: 50066-208 | Form: CREAM
Manufacturer: Genomma Lab USA, Inc.
Category: otc | Type: HUMAN OTC DRUG LABEL
Date: 20250702

ACTIVE INGREDIENTS: TERBINAFINE HYDROCHLORIDE 1 g/100 g
INACTIVE INGREDIENTS: BENZYL ALCOHOL; CETYL ALCOHOL; CETYL PALMITATE; ISOPROPYL MYRISTATE; POLYSORBATE 60; WATER; SODIUM HYDROXIDE; SORBITAN MONOSTEARATE; STEARYL ALCOHOL

Silka®
Jock Itch

Drug Facts

Active ingredient

Terbinafine hydrochloride 1%

Purpose

Antifungal

Uses

- cures most jock itch (tinea cruris)
- relieves itching, burning, cracking and scaling which accompany this condition

Warnings

For external use only

Do not use

- on nails or scalp
- in or near the mouth or eyes
- for vaginal yeast infections

WHEN USING

When using this productdo not get into eyes. If eye contact occurs, rinse thoroughly with water.

Stop use and ask a doctor iftoo much irritation occurs or gets worse

Keep out of reach of children.If swallowed, get medical help or contact a Poison Control Center right away.

Directions

- adults and children 12 years and over:
  - use the tip of the cap to break the seal and open the tube
  - wash the affected skin with soap and water and dry completely before applying
  - apply once a day (morning ornight) for 1 weekor as directed by a doctor
  - wash hands after each use
- children under 12 years: ask a doctor

Other information

- do not use if seal on tube is broken or is not visible
- store at controlled room temperature 20° to 25°C (68° to 77°F)
- see carton or tube crimp for lot number and expiration date

Inactive ingredients

benzyl alcohol, cetyl alcohol, cetyl palmitate, isopropyl myristate, polysorbate 60, purified water, sodium hydroxide, sorbitan monostearate, stearyl alcohol

Questions?

call 1 877 99 GENOM (43666)

Distributed by:
Genomma Lab USA Inc., Houston, TX, 77027

PRINCIPAL DISPLAY PANEL - 15 g Tube Carton

SILKA®
Terbinafine Hydrochloride Cream 1%
ANTIFUNGAL CREAM

FULL PRESCRIPTION
STRENGTH

JOCK ITCH

CURES MOST JOCK ITCH
NET WT 0.5 oz (15 g)